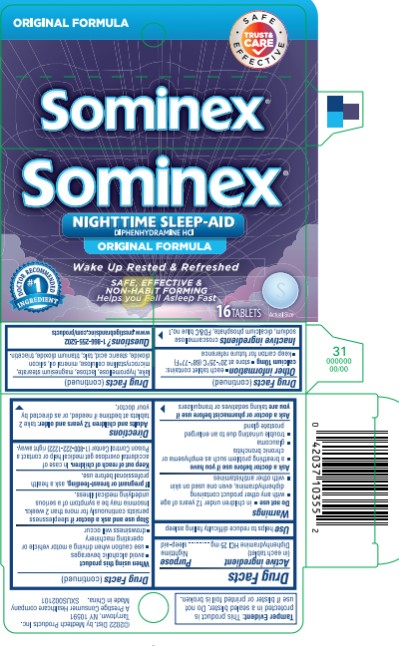 DRUG LABEL: Sominex
NDC: 63029-554 | Form: TABLET, FILM COATED
Manufacturer: Medtech Products Inc.
Category: otc | Type: HUMAN OTC DRUG LABEL
Date: 20251023

ACTIVE INGREDIENTS: DIPHENHYDRAMINE HYDROCHLORIDE 25 mg/1 1
INACTIVE INGREDIENTS: CALCIUM PHOSPHATE, DIBASIC, DIHYDRATE; CELLULOSE, MICROCRYSTALLINE; CROSCARMELLOSE SODIUM; FD&C BLUE NO. 1; HYPROMELLOSE, UNSPECIFIED; LACTOSE MONOHYDRATE; LIGHT MINERAL OIL; MAGNESIUM STEARATE; SILICON DIOXIDE; STEARIC ACID; TALC; TITANIUM DIOXIDE; TRIACETIN

Sominex-Original

Drug Facts

Active ingredient

(in each caplet)

Diphenhydramine HCl 25 mg

Purpose

Nighttime sleep-aid

Use

helps reduce difficultly falling asleep

Warnings

Do not use

- in children under 12 years of age
- with any other product containing diphenhydramine, even one used on skin
- with other antihistamines

Ask a doctor before use if you have

- a breathing problem such as emphysema or chronic bronchitis
- glaucoma
- trouble urinating due to an enlarged prostate gland

Ask a doctor or pharmacist before use if you are

taking sedatives or tranquilizers

When using this product

- avoid alcoholic beverages

- be careful when driving a motor vehicle or operating machinery
- drowsiness will occur

Stop use and ask a doctor if

sleeplessness persists continuously for more than 2 weeks. Insomnia may be a symptom of serious underlying medical illness.

If pregnant or breast-feeding,

ask a health professional before use.

Keep out of reach of children.

In case of overdose, get medical help or contact a Poison Control Center (1-800-222-1222) right away.

Directions

- adults and children 12 years and older: take 2 tablets at bedtime if needed, or as directed by your doctor

Other information

store at room temperature 20º- 25ºC (68º-77ºF)

Inactive ingredients

croscarmellose sodium, dicalcium phosphate, FD&C blue no. 1 lake, hypromellose, lactose, magnesium stearate, microcrystalline cellulose, mineral oil, silica, stearate acid, talc, titanium dioxide, triacetin

Questions?

1-866-255-5202

PRINCIPAL DISPLAY PANEL

MAXIMUM STRENGTH FORMULA
Sominex®
NIGHTTIME SLEEP-AID DIPHENHYDRAMINE HCl
16 TABLETS